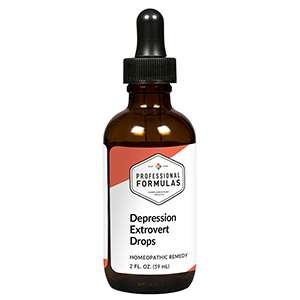 DRUG LABEL: Melancholy Drops Extrovert
NDC: 63083-2015 | Form: LIQUID
Manufacturer: Professional Complementary Health Formulas
Category: homeopathic | Type: HUMAN OTC DRUG LABEL
Date: 20190815

ACTIVE INGREDIENTS: CAULOPHYLLUM THALICTROIDES ROOT 3 [hp_X]/59 mL; PULSATILLA MONTANA WHOLE 4 [hp_X]/59 mL; BLACK COHOSH 6 [hp_X]/59 mL; FERULA ASSA-FOETIDA RESIN 12 [hp_X]/59 mL; SODIUM CHLORIDE 12 [hp_X]/59 mL; LACHESIS MUTA VENOM 16 [hp_X]/59 mL; SEPIA OFFICINALIS JUICE 16 [hp_X]/59 mL; HUMAN CHOLECYSTOKININ-33 30 [hp_X]/59 mL
INACTIVE INGREDIENTS: ALCOHOL; WATER

C15

ACTIVE INGREDIENTS

Caulophyllum thalictroides 3X, 6X, 12X, 60X
Pulsatilla 4X
Cimicifuga racemosa 6X
Asafoetida 12X
Natrum muriaticum 12X
Lachesis mutus 16X
Sepia 16X, 30X, 60X
Cholecystokinin (CCK) 30X, 60X

QUESTIONS

Professional Formulas

PO Box 2034 Lake Oswego, OR 97035

INDICATIONS

For the temporary relief of sadness or fatigue, particularly in those with extroverted personality.*

PURPOSE

*Claims based on traditional homeopathic practice, not accepted medical evidence. Not FDA evaluated.

WARNINGS

Persistent symptoms may be a sign of a serious condition. If symptoms persist or worsen, consult a doctor. Keep out of the reach of children. In case of overdose, get medical help or contact a poison control center right away. If pregnant or breastfeeding, ask a healthcare professional before use.

Keep out of the reach of children.

PREGNANCY OR BREAST FEEDING

If pregnant or breastfeeding, ask a healthcare professional before use.

DIRECTIONS

Place drops under tongue 30 minutes before/after meals. Adults and children 12 years and over: Take 10 drops up to 3 times per day. Consult a physician for use in children under 12 years of age.

OTHER INFORMATION

Tamper resistant. If seal is broken, do not use. After opening, close container tightly and store at room temperature away from heat.

INACTIVE INGREDIENTS

20% ethanol, purified water.

LABEL

Est 1985

Professional Formulas

Complementary Health

Melancholy Drops Extrovert

Homeopathic Remedy

2 FL. OZ. (59 mL)